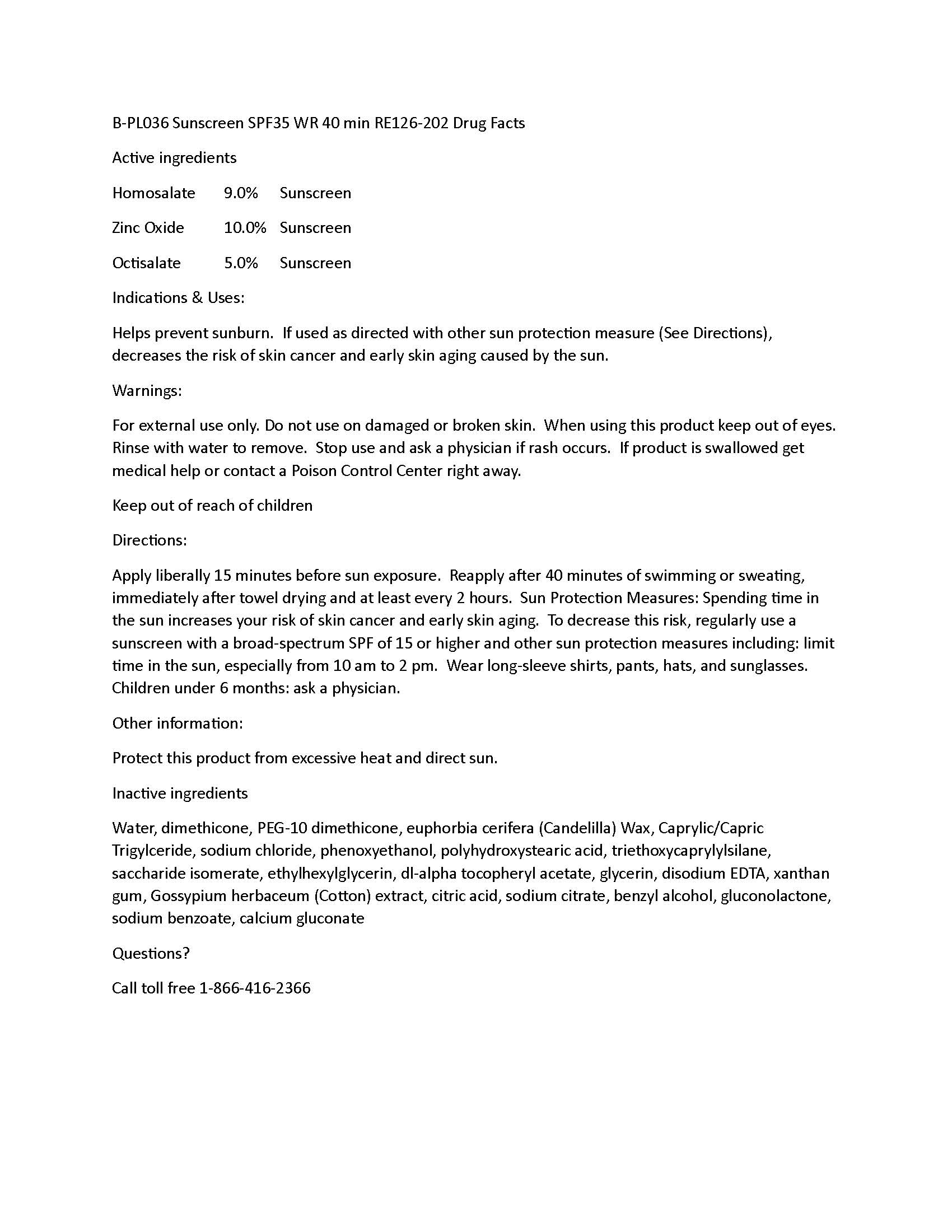 DRUG LABEL: Private Label Sunscreen SPF35 40min WR RE126-202
NDC: 60232-0036 | Form: LOTION
Manufacturer: Swiss-American CDMO, LLC
Category: otc | Type: HUMAN OTC DRUG LABEL
Date: 20231109

ACTIVE INGREDIENTS: HOMOSALATE 90 g/1000 g; ZINC OXIDE 100 g/1000 g; OCTISALATE 50 g/1000 g
INACTIVE INGREDIENTS: WATER; EDETATE DISODIUM; SODIUM CHLORIDE; XANTHAN GUM; PHENOXYETHANOL; ETHYLHEXYLGLYCERIN; MEDIUM-CHAIN TRIGLYCERIDES; DIMETHICONE; .ALPHA.-TOCOPHEROL ACETATE; POLYHYDROXYSTEARIC ACID (2300 MW); TRIETHOXYCAPRYLYLSILANE; CANDELILLA WAX; PEG-10 DIMETHICONE (220 CST); SACCHARIDE ISOMERATE; GLYCERIN; GOSSYPIUM HIRSUTUM WHOLE

Private Label Sunscreen SPF35 40min WR RE126-202

Warnings

For external use only. Do not use on damaged or broken skin. When using this product keep out of eyes. Rinse with water to remove. Stop use and ask a physician if rash occurs. If product is swallowed get medical help or contact a Poison Control Center right away.

Active Ingredients

Homosalate 9.0% Sunscreen
Zinc Oxide 10.0% Sunscreen
Octisalate 5.0% Sunscreen

uses

Helps prevent sunburn. If used as directed with other sun protection measure (See Directions), decreases the risk of skin cancer and early skin aging caused by the sun.

uses

Helps prevent sunburn. If used as directed with other sun protection measure (See Directions), decreases the risk of skin cancer and early skin aging caused by the sun.

Directions

Apply liberally 15 minutes before sun exposure. Reapply after 40 minutes of swimming or sweating, immediately after towel drying and at least every 2 hours. Sun Protection Measures: Spending time in the sun increases your risk of skin cancer and early skin aging. To decrease this risk, regularly use a sunscreen with a broad-spectrum SPF of 15 or higher and other sun protection measures including: limit time in the sun, especially from 10 am to 2 pm. Wear long-sleeve shirts, pants, hats, and sunglasses. Children under 6 months: ask a physician.

Keep out of reach of children

Other information:

Protect this product from excessive heat and direct sun.

Inactive Ingredients

Water, dimethicone, PEG-10 dimethicone, euphorbia cerifera (Candelilla) Wax, Caprylic/Capric Trigylceride, sodium chloride, phenoxyethanol, polyhydroxystearic acid, triethoxycaprylylsilane, saccharide isomerate, ethylhexylglycerin, dl-alpha tocopheryl acetate, glycerin, disodium EDTA, xanthan gum, Gossypium herbaceum (Cotton) extract, citric acid, sodium citrate, benzyl alcohol, gluconolactone, sodium benzoate, calcium gluconate

Questions?

Call toll free 1-866-416-2366